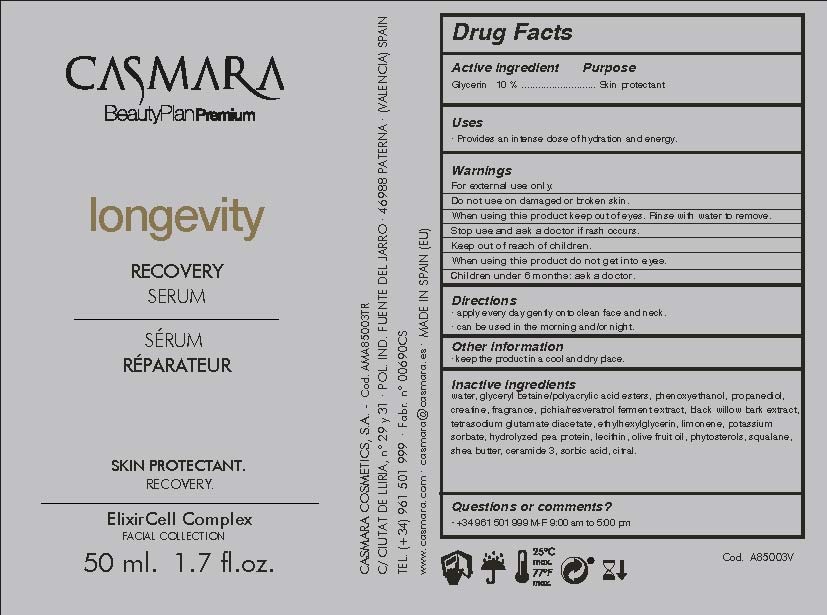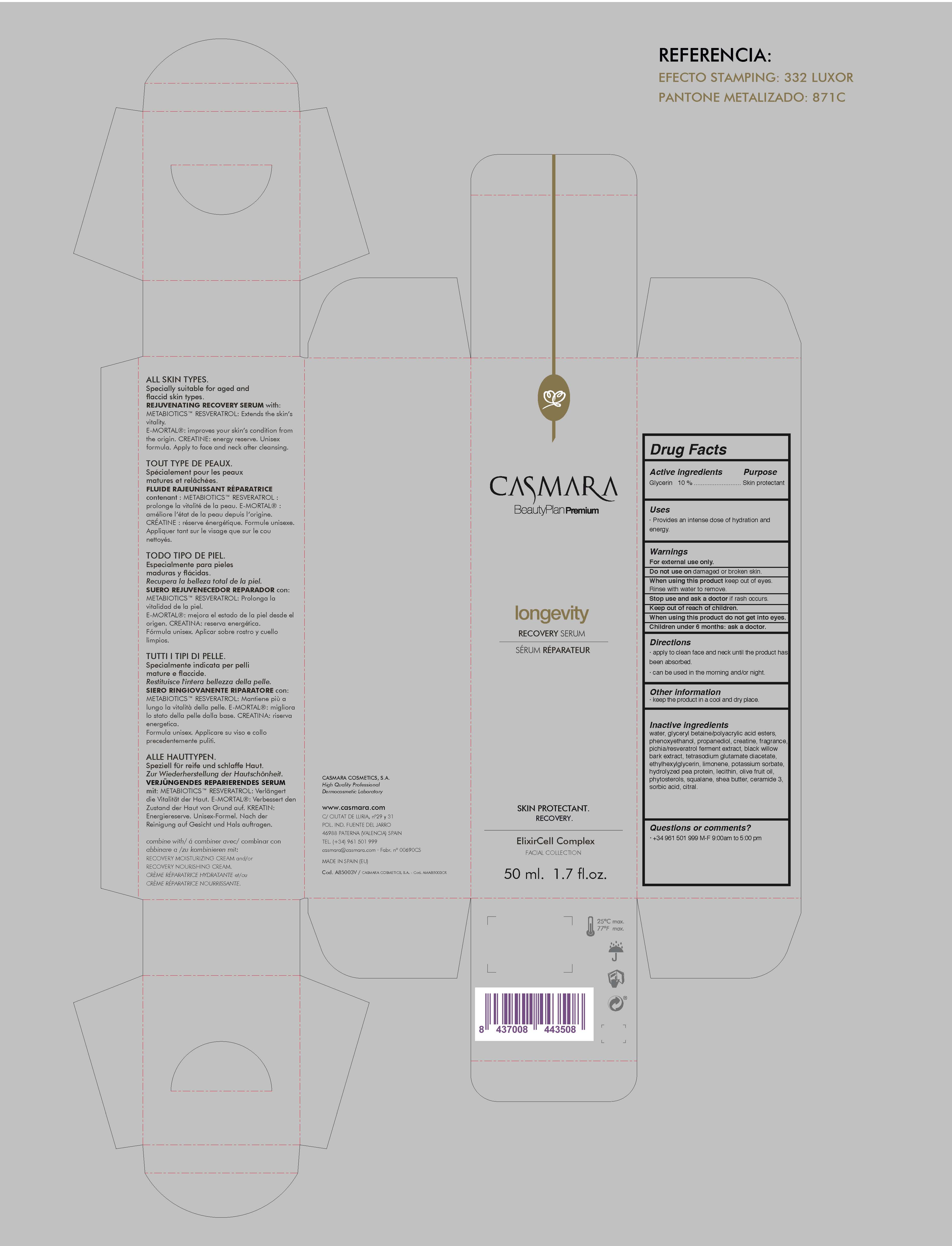 DRUG LABEL: Longevity Recovery Serum
NDC: 20151-098 | Form: CREAM
Manufacturer: Casmara Cosmetics, SA
Category: otc | Type: HUMAN OTC DRUG LABEL
Date: 20170330

ACTIVE INGREDIENTS: GLYCERIN 10 mg/1 mL
INACTIVE INGREDIENTS: CREATINE 0.5 mg/1 mL; WILLOW BARK 0.125 mg/1 mL; CITRAL 0.00125 mg/1 mL; SOY STEROL 0.01 mg/1 mL; POTASSIUM SORBATE 0.012 mg/1 mL; SORBIC ACID 0.0012 mg/1 mL; ETHYLHEXYLGLYCERIN 0.08 mg/1 mL; WATER 77.044 mg/1 mL; PROPANEDIOL 0.75 mg/1 mL; PHENOXYETHANOL 0.9 mg/1 mL; TETRASODIUM GLUTAMATE DIACETATE 0.094 mg/1 mL; CYBERLINDNERA JADINII 0.225 mg/1 mL; PEA PROTEIN 0.01 mg/1 mL; LIMONENE, (+)- 0.017 mg/1 mL; OLIVE OIL 0.01 mg/1 mL; SQUALANE 0.01 mg/1 mL; SHEA BUTTER 0.01 mg/1 mL; CERAMIDE 3 0.01 mg/1 mL; HYDROGENATED SOYBEAN LECITHIN 0.01 mg/1 mL; BETAINE 9.9 mg/1 mL

Longevity Recovery Serum

ACTIVE INGREDIENTS PURPOSE

Glycerin 10%.................... Skin Protectant

Warnings

For external use only.

Do not use on damaged or broken skin.

When using this product keep our of the eyes. Rinse with water to remove.

Stop use and ask a doctor if rash occurs.

Keep out of reach of children.

Whhen using this product do not get into eyes.

Children under 6 months: as a doctor.

WARNINGS

Stop use and ask a doctor if rash occurs

Children under 6 months: ask a doctor

Warnings

Keep out of reach of children

Questions or comments?

+ 34 961 501 999 M-F 9:00 am to 5:00 pm

Other Information

. keep the product in a cool and dry place

Directions

. apply every day gently onto clean face and neck

. can be used in the morning and/or night

DOSAGE AND ADMINISTRATION

- apply every day gently onto clean face and neck
- .can be used in the morning and/or night

Uses

. provides an intense dose of hydration and energy

Inactive Ingredients

Water, betaine, Phenoxyethanol, propanediol, Creatine, Fragrance, Pichia, resveratrol ferment extract, Black Willow bark extract, Tetrasodium glutamate diacetate, Ethylhexylglycerin, Limonene, Potassium sorbate, Hydrolyzed pea protein, Lecithin, Olive fruit oil, Phytosterols, Squalane, Shea butter , Ceramide 3, Sorbic acid, Citral

Uses

. provides an intense dose of hydration and energy